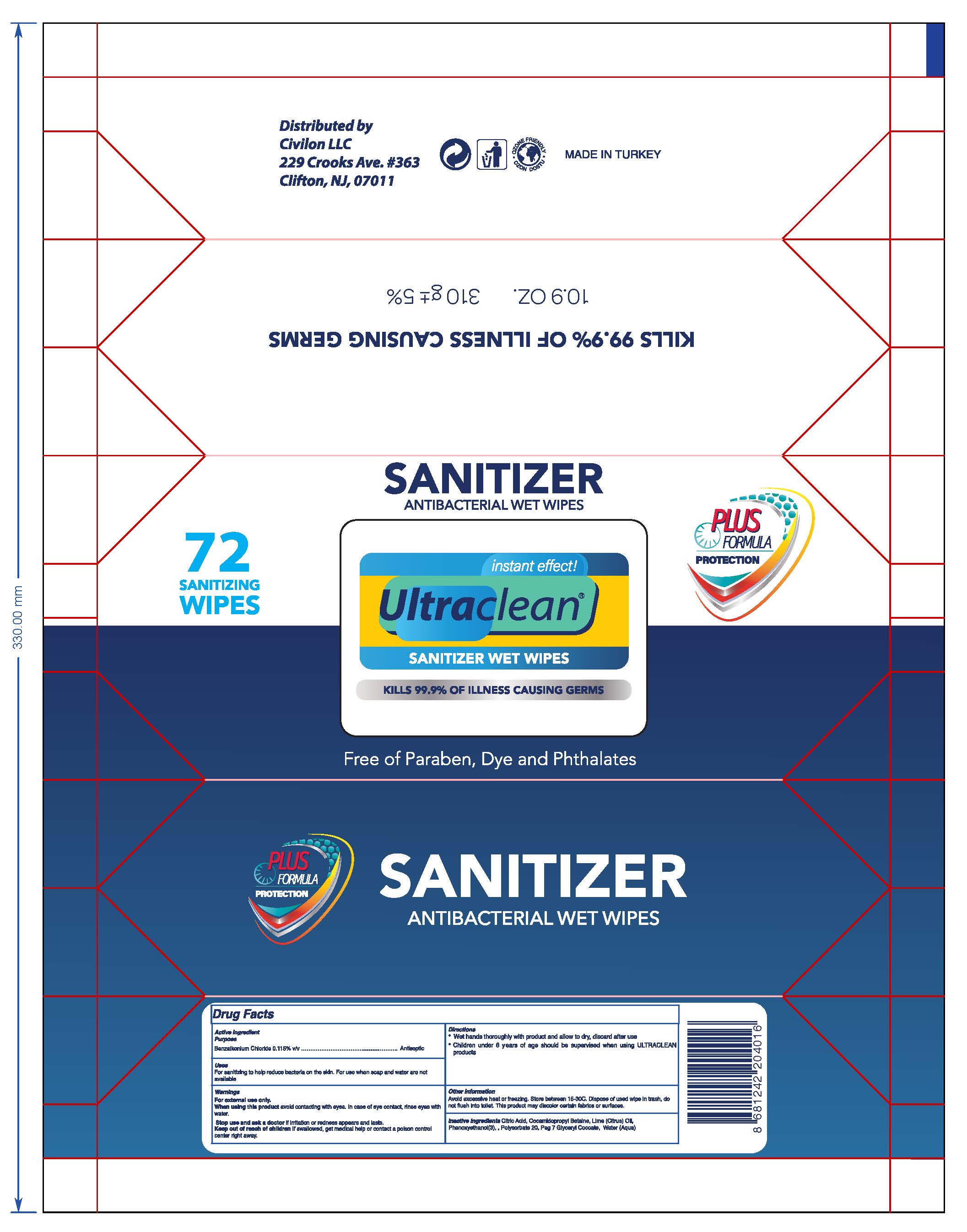 DRUG LABEL: UltraClean
NDC: 77222-224 | Form: SWAB
Manufacturer: SIRIUS ENDUSTRI YATIRIMLARI VE PLASTIK SANAYI ANONIM SIRKETI
Category: otc | Type: HUMAN OTC DRUG LABEL
Date: 20200620

ACTIVE INGREDIENTS: BENZALKONIUM CHLORIDE 0.115 mg/1 mL
INACTIVE INGREDIENTS: PHENOXYETHANOL; COCAMIDOPROPYL BETAINE; CITRIC ACID MONOHYDRATE; LIME OIL; WATER; POLYSORBATE 20; PEG-7 GLYCERYL COCOATE

SIRIUS-UltrClean Wet Wipes

Active Ingredient(s)

Benzalkonium chloride 0.115%

Purpose

Antiseptic

Use

For sanitizing to help reduce bacteria on the skin. For use when soap and water are not available.

Warnings

For external use only. Flammable. Keep away from heat or flame.

Not edible, don't drink. Do not use in ears or mouth.

When using this product keep out of eyes, ears, and mouth. In case of contact with eyes, rinse eyes thoroughly with water.
Stop use and ask a doctor if irritation or rash occurs. These may be signs of a serious condition.
Keep out of reach of children. If swallowed, get medical help or contact a Poison Control Center right away.

Stop use and ask a doctor if irritation or rash occurs. These may be signs of a serious condition.

Keep out of reach of children. If swallowed, get medical help or contact a Poison Control Center right away.

Directions

Wet hands thoroughly with the product and allow it to dry, discard after use.

Children under 6 years of age should be supervised when using UltraClean Products.

Other information

- Avoid excessive heat or freezing. Store between 15-30 C.
- Dispose the used wipe in trash, do not flush it into the toilet.
- The product may discolor certain fabrics or surfaces.

Inactive ingredients

Water, citric acid, lime oil, Cocamidopropyl betaine, Phenoxyethanol, Polysorbate 20, peg-7 glyceryl cocoate

Package Label - Principal Display Panel

72 PCS NDC: 77222-224-01